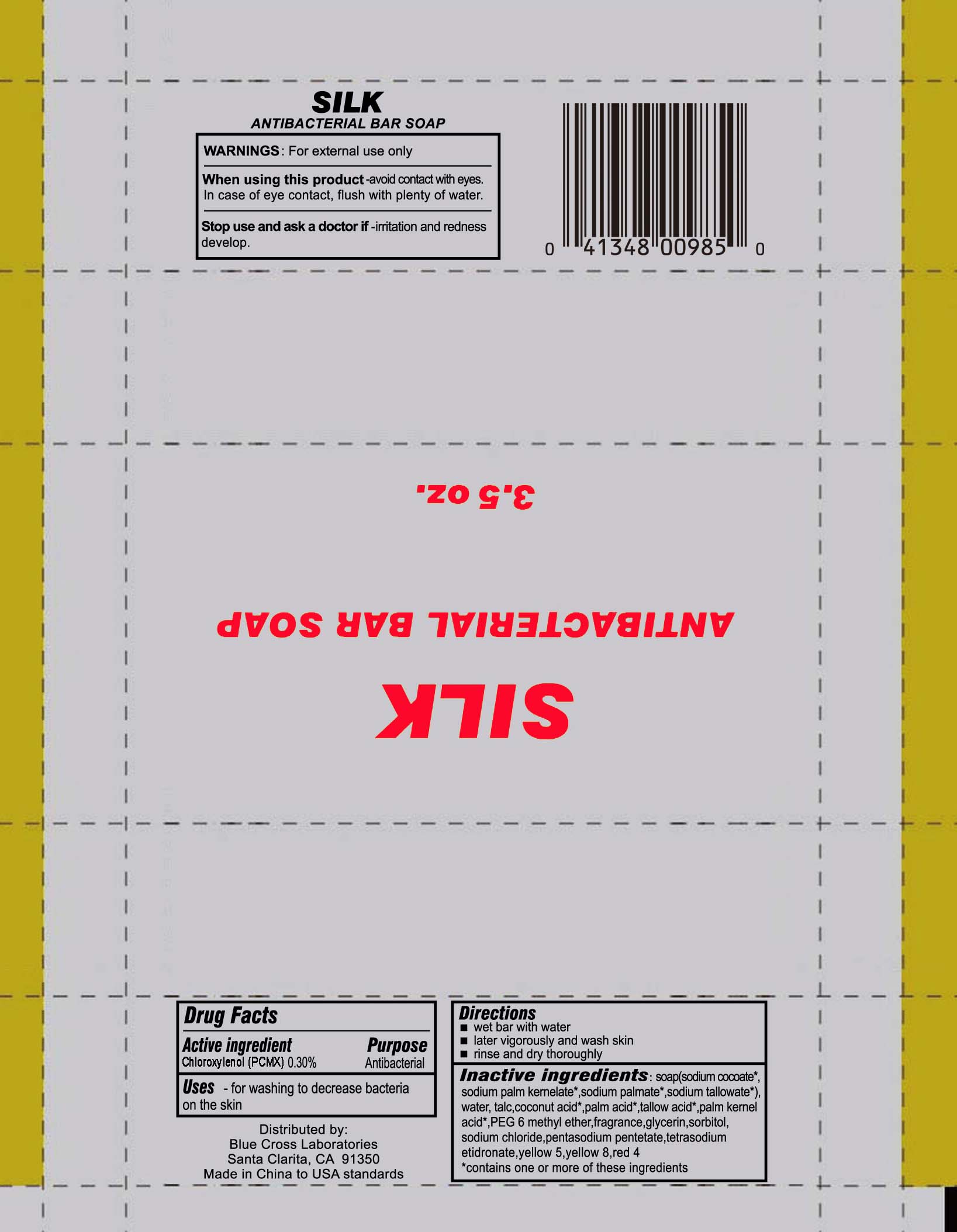 DRUG LABEL: Antibacterial Bar
NDC: 22431-701 | Form: SOAP
Manufacturer: Blue Cross Laboratories, Inc
Category: otc | Type: HUMAN OTC DRUG LABEL
Date: 20170127

ACTIVE INGREDIENTS: CHLOROXYLENOL .3 g/100 g
INACTIVE INGREDIENTS: SODIUM COCOATE; SODIUM PALM KERNELATE; SODIUM PALMATE; SODIUM TALLOWATE, BEEF; WATER; TALC; COCONUT ACID; PALM ACID; TALLOW ACID, BEEF; PALM KERNEL ACID; PEG-6 METHYL ETHER; GLYCERIN; SORBITOL; SODIUM CHLORIDE; PENTASODIUM PENTETATE; ETIDRONATE TETRASODIUM; FD&C YELLOW NO. 5; FLUORESCEIN SODIUM; FD&C RED NO. 4

Silk Antibacterial Bar Soap

ACTIVE INGREDIENT

Chloroxylenol (PCMX) 0.30% .............. Antibacterial

PURPOSE

for washing to decrease bacteria on the skin

Keep out of reach of children

Stop use and ask a doctor if - irritation and redness develop

WARNINGS

For external use only

When using this product - avoid contact with eyes. In case of eye contact, flush with plenty of water.

DOSAGE AND ADMINISTRATION

- wet bar with water
- later vigorously and wash skin
- rinse and dry thoroughly

INACTIVE INGREDIENT

Soap (sodium cocoate, sodium palm kernelate sodium palmate, sodium tallowate), water, talc, coconut acid, palm acid, tallow acid, palm kernel acid, PEG-6 methyl ether, fragrance, glycerin, sorbitol, sodium chloride, pentasodium, pentetate, tetrasodium etidronate, yellow 5, yellow 8, red 4

PACKAGE LABEL

SILK

Antibacterial Bar Soap

3.5 oz.